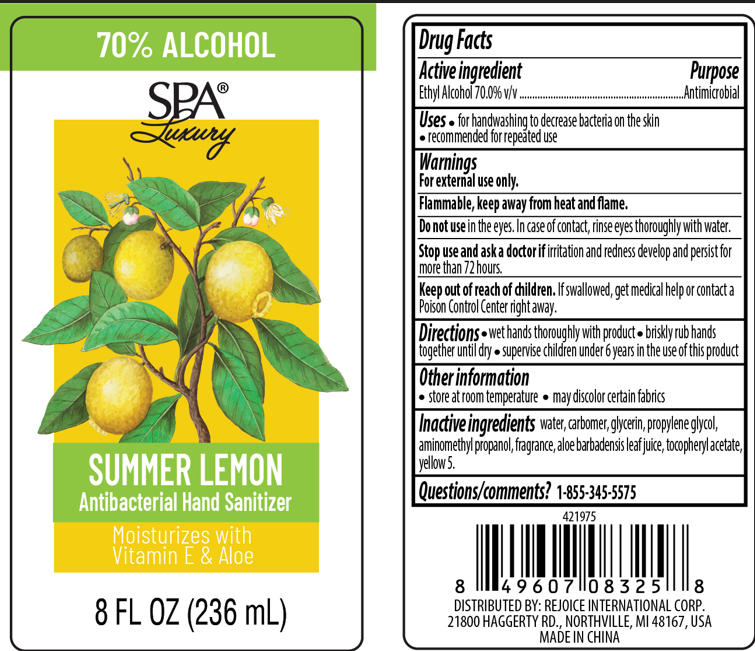 DRUG LABEL: SPA HAND SANITIZER SUMMER LEMON
NDC: 57337-189 | Form: GEL
Manufacturer: Rejoice International Corp.
Category: otc | Type: HUMAN OTC DRUG LABEL
Date: 20260120

ACTIVE INGREDIENTS: ALCOHOL 70 mL/100 mL
INACTIVE INGREDIENTS: WATER; GLYCERIN; YELLOW 5; .ALPHA.-TOCOPHEROL ACETATE; ALOE BARBADENSIS LEAF JUICE; CARBOMER; PROPYLENE GLYCOL; AMINOMETHYL PROPANOL

SPA HAND SANITIZER SUMMER LEMON

Active ingredient

Ethyl Alcohol 70.0% v/v

Uses

- for handwashing to decrease bacteria on the skin
- recommended for repeated use

Warnings

For external use only

Flammable, keep away from heat and flame.

Do not use in the eyes. In case of contact, rinse eyes thoroughly with water.

Stop use and ask a doctor if irritation and redness develop and persist for more than 72 hours.

Keep out of reach of children

If swallowed, get medical help or contact a Poison Control Center right away.

Directions

- wet hands thoroughly with product
- briskly rub hands together until dry
- supervise children under 6 years in the use of this product

Other information

- store at room temperature
- may discolor certain fabrics

Inactive ingredients

Water

Carbomer

Glycerin

Propylene Glycol

Aminomethyl Propanol

Fragrance

Aloe Barbadensis Leaf Juice

Tocopheryl Acetate

Yellow 5

Purpose

Antimicrobial